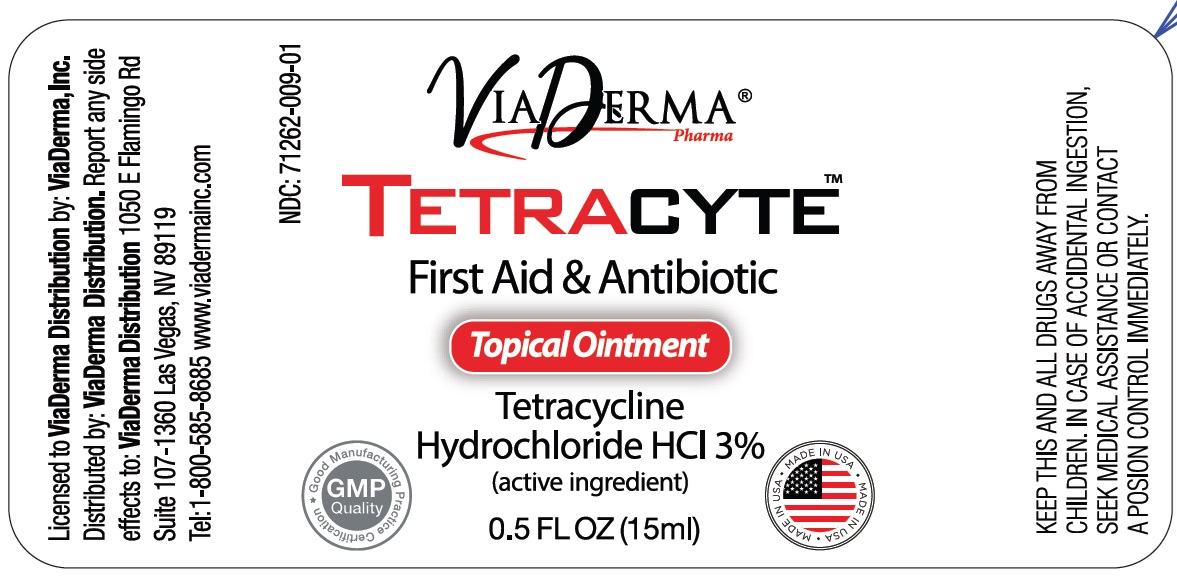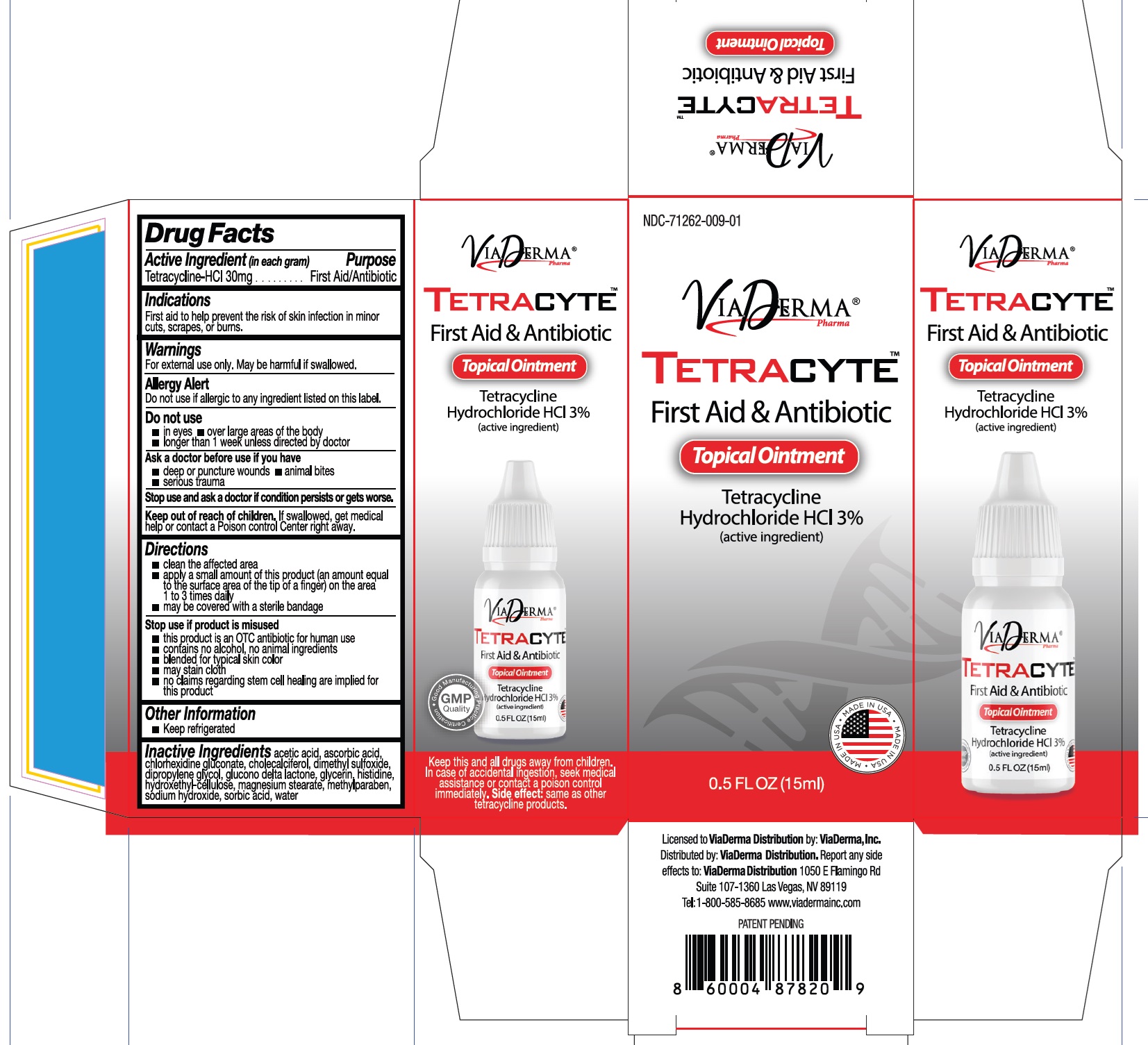 DRUG LABEL: Tetracyte Topical Tetracycline Hydrochloride
NDC: 71262-009 | Form: OINTMENT
Manufacturer: VIADERMA DISTRIBUTION INC
Category: otc | Type: HUMAN OTC DRUG LABEL
Date: 20240801

ACTIVE INGREDIENTS: TETRACYCLINE HYDROCHLORIDE 30 mg/1 mL
INACTIVE INGREDIENTS: ACETIC ACID; ASCORBIC ACID; CHLORHEXIDINE GLUCONATE; CHOLECALCIFEROL; DIMETHYL SULFOXIDE; DIPROPYLENE GLYCOL; GLUCONOLACTONE; GLYCERIN; HISTIDINE; HYDROXYETHYL CELLULOSE, UNSPECIFIED; MAGNESIUM STEARATE; METHYLPARABEN; SODIUM HYDROXIDE; SORBIC ACID; WATER

Tetracyte Topical Ointment Tetracycline Hydrochloride

Active Ingredient (in each gram)

Tetracycline-HCl 30mg

Purpose

First Aid/Antibiotic

Indications

First aid to help prevent the risk of skin infection in minor cuts, scrapes, or burns.

Warnings

For external use only. May be harmful if swallowed.

Allergy Alert

Do not use if allergic to any ingredient listed on this label.

Do not use

- in eyes
- over large areas of the body
- longer than 1 week unless directed by doctor

Ask a doctor before use if you have

- deep or puncture wounds
- animal bites
- serious trauma

Stop use and ask a doctor

if condition persists or gets worse.

Keep out of reach of children.

If swallowed, get medical help or contact a Poison control Center right away.

Directions

- clean the affected area
- apply a small amount of this product (an amount equal to the surface area of the tip of a finger) on the area 1 to 3 times daily
- may be covered with a sterile bandage

Stop use if product is misused

- this product is an OTC antibiotic for human use
- contains no alcohol, no animal ingredients
- blended for typical skin color
- may stain cloth
- no clamis regarding stem cell healing are implied for this product

Other Information

- Keep refrigerated

Inactive Ingredients

acetic acid, ascorbic acid, chlorhexidine gluconate, cholecalciferol, dimethyl sulfoxide, dipropylene glycol, glucono delta lactone, glycerin, histidine, hydroxethyl-cellulose, magnesium stearate, methylparaben, sodium hydroxide, sorbic acid, water